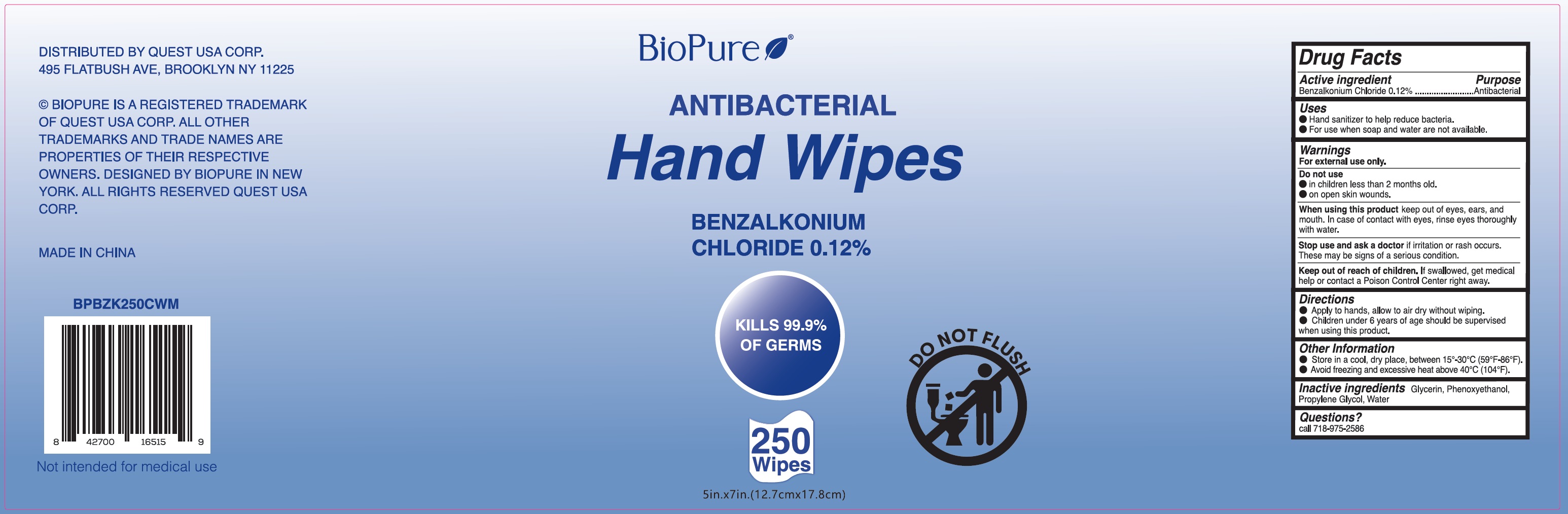 DRUG LABEL: BioPure Antibacterial Hand Wipes Benzalkonium Chloride 0.12% - 250 Wipes
NDC: 78691-009 | Form: CLOTH
Manufacturer: QUEST USA CORP.
Category: otc | Type: HUMAN OTC DRUG LABEL
Date: 20251231

ACTIVE INGREDIENTS: BENZALKONIUM CHLORIDE 1.2 mg/1 mL
INACTIVE INGREDIENTS: GLYCERIN; PHENOXYETHANOL; PROPYLENE GLYCOL; WATER

BioPure Antibacterial Hand Wipes Benzalkonium Chloride 0.12% - 250 Wipes

Active ingredient

Benzalkonium Chloride 0.12%

Purpose

Antibacterial

Uses

• Hand sanitizer to help reduce bacteria. • For use when soap and water are not available.

Warnings

For external use only.

Do not use

• in children less than 2 months old. • on open skin wounds.

When using this product

keep out of eyes, ears, and mouth. In case of contact with eyes, rinse eyes thoroughly with water.

Stop use and ask a doctor if

irritation or rash occurs. These may be signs of a serious condition.

Keep out of reach of children.

If swallowed, get medical help or contact a Poison Control Center right away.

Directions

• Apply to hands, allow to air dry without wiping. • Children under 6 years of age should be supervised when using this product.

Other information

• Store in a cool, dry place, between 15°-30° (59°-86°F). • Avoid freezing and excessive heat above 40°C (104°F).

Inactive ingredients

Glycerin, Phenoxyethanol, Propylene Glycol, Purified Water

Questions?

call 718-975-2586